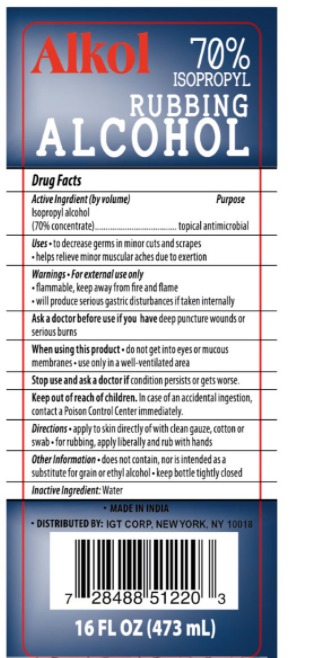 DRUG LABEL: RUBBING ALCOHOL
NDC: 78440-010 | Form: LIQUID
Manufacturer: INTERNATIONAL GENERAL TRADING CORP
Category: otc | Type: HUMAN OTC DRUG LABEL
Date: 20241218

ACTIVE INGREDIENTS: ISOPROPYL ALCOHOL 70 mL/100 mL
INACTIVE INGREDIENTS: WATER

RUBBING ALCOHOL 70%

Active Ingredient(s)

ALCPHOL 70

Purpose

ANTIMICROBIAL

Use

DECREASE GERMS

Warnings

For external use only. Flammable. Keep away from heat or flame

Do not use

- in children less than 2 months of age
- on open skin wounds

When using this product keep out of eyes, ears, and mouth. In case of contact with eyes, rinse eyes thoroughly with water.
Stop use and ask a doctor if irritation or rash occurs. These may be signs of a serious condition.
Keep out of reach of children. If swallowed, get medical help or contact a Poison Control Center right away.

Stop use and ask a doctor if irritation or rash occurs. These may be signs of a serious condition.

Keep out of reach of children. If swallowed, get medical help or contact a Poison Control Center right away.

Directions

- Place enough product on hands to cover all surfaces. Rub hands together until dry.
- Supervise children under 6 years of age when using this product to avoid swallowing.

Other information

- Store between 15-30C (59-86F)
- Avoid freezing and excessive heat above 40C (104F)

Inactive ingredients

WATER

Package Label - Principal Display Panel

78440-010-01